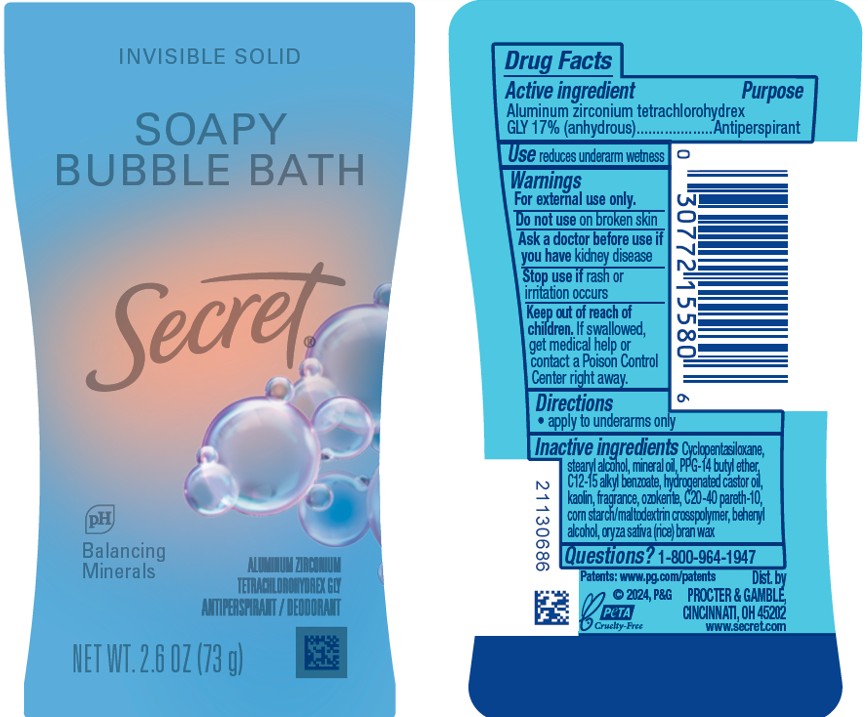 DRUG LABEL: Secret Soapy Bubble Bath Invisible
NDC: 84126-189 | Form: STICK
Manufacturer: The Procter & Gamble Manufacturing Company
Category: otc | Type: HUMAN OTC DRUG LABEL
Date: 20251029

ACTIVE INGREDIENTS: ALUMINUM ZIRCONIUM TETRACHLOROHYDREX GLY 17 g/100 g
INACTIVE INGREDIENTS: CERESIN; CYCLOPENTASILOXANE; STEARYL ALCOHOL; MINERAL OIL; HYDROGENATED CASTOR OIL; PPG-14 BUTYL ETHER; C20-40 PARETH-10; BEHENYL ALCOHOL; KAOLIN; C12-15 ALKYL BENZOATE; ORYZA SATIVA (RICE) BRAN

Secret Soapy Bubble Bath Invisible Solid

Drug Facts

Active ingredient

Aluminum zirconium tetrachlorohydrex Gly 17% (anhydrous)

Purpose

Antiperspirant

Use

reduces underarm wetness

Warnings

For external use only.

Do not use on broken skin

Ask a doctor before use if you have kidney disease

Stop use if rash or irritation occurs

Keep out of reach of children. If swallowed, get medical help or contact a Poison Control Center right away.

Directions

apply to underarms only

Inactive ingredients

Cyclopentasiloxane, stearyl alcohol, mineral oil, PPG-14 butyl ether, C12-15 alkyl benzoate, hydrogenated castor oil, kaolin, fragrance, ozokerite, C20-40 pareth-10, corn starch/maltodextrin crosspolymer, behenyl alcohol, oryza sativa (rice) bran wax

Questions?

1-800-964-1947

www.secret.com

Dist. by PROCTER & GAMBLE,
CINCINNATI, OH 45202.

www.secret.com

PRINCIPAL DISPLAY PANEL - 73 g Canister Label

INVISIBLE SOLID

SOAPY BUBBLE BATH

Secret®

pH Balancing Minerals

ALUMINUM ZIRCONIUM TETRACHLOROHYDREX GLY

ANTIPERSPIRANT / DEODORANT

NET WT. 2.6 OZ